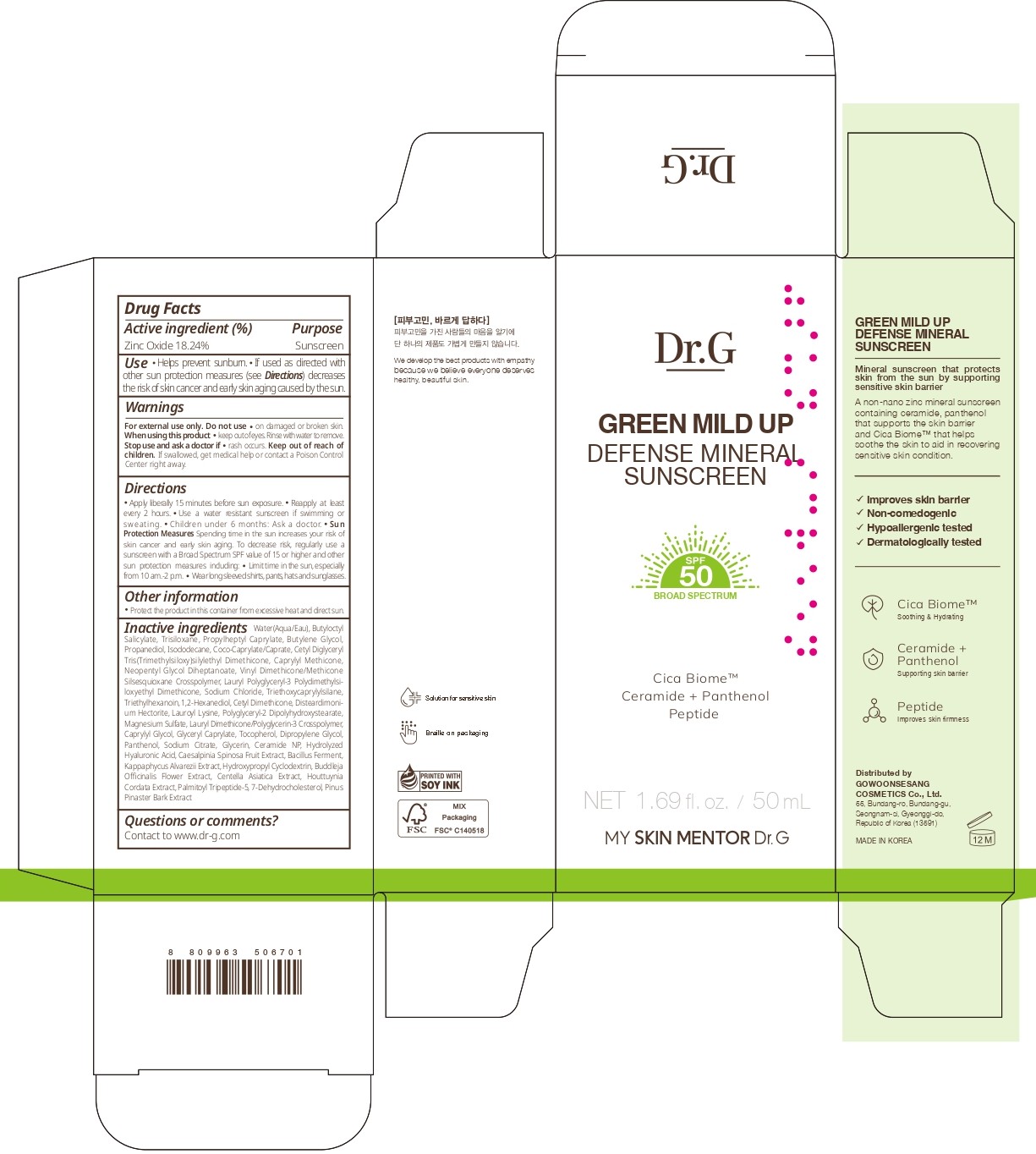 DRUG LABEL: Dr.G GREEN MILD UP DEFENSE MINERAL SUNSCREEN
NDC: 51621-022 | Form: CREAM
Manufacturer: GOWOONSESANG COSMETICS CO., LTD.
Category: otc | Type: HUMAN OTC DRUG LABEL
Date: 20250321

ACTIVE INGREDIENTS: ZINC OXIDE 18.24 g/100 mL
INACTIVE INGREDIENTS: TARA SPINOSA FRUIT; HOUTTUYNIA CORDATA FLOWERING TOP; WATER; CAPRYLYL GLYCOL; TRISILOXANE; CAPRYLYL METHICONE; LAUROYL LYSINE; BUDDLEJA OFFICINALIS FLOWER; GLYCERYL CAPRYLATE; DIPROPYLENE GLYCOL; HYDROXYPROPYL BETADEX; SODIUM CITRATE; BUTYLENE GLYCOL; MAGNESIUM SULFATE; ISODODECANE; VINYL DIMETHICONE/METHICONE SILSESQUIOXANE CROSSPOLYMER; SODIUM CHLORIDE; 1,2-HEXANEDIOL; POLYGLYCERYL-2 DIPOLYHYDROXYSTEARATE; KAPPAPHYCUS ALVAREZII; TOCOPHEROL; GLYCERIN; PALMITOYL TRIPEPTIDE-5; COCO-CAPRYLATE/CAPRATE; TRIETHYLHEXANOIN; PANTHENOL; CERAMIDE NP; MARITIME PINE; PROPYLHEPTYL CAPRYLATE; NEOPENTYL GLYCOL DIHEPTANOATE; DISTEARDIMONIUM HECTORITE; CENTELLA ASIATICA TRITERPENOIDS; 7-DEHYDROCHOLESTEROL; BUTYLOCTYL SALICYLATE; TRIETHOXYCAPRYLYLSILANE; PROPANEDIOL

Active ingredient

Zinc Oxide 18.24%

Purpose

Sunscreen

Use

- Helps prevent sunburn.
- If used as directed with other sun protection measures (see Directions) decreases the risk of skin cancer and early skin aging caused by the sun.

Warnings

For external use only. Do not use

- on damaged or broken skin.

When using this product

- keep out of eyes. Rinse with water to remove.

Stop use and ask a doctor if

- rash occurs.

Keep out of reach of children.

If swallowed, get medical help or contact a Poison Control Center right away.

Directions

- Apply liberally 15 minutes before sun exposure.
- Reapply at least every 2 hours.
- Use a water resistant sunscreen if swimming or sweating.
- Children under 6 months: Ask a doctor.
- Sun Protection Measures Spending time in the sun increases your risk of skin cancer and early skin aging. To decrease risk, regularly use a sunscreen with a Broad Spectrum SPF value of 15 or higher and other sun protection measures including:
- Limit time in the sun, especially from 10 am .- 2 p.m.
- Wear long sleeved shirts, pants, hats and sunglasses.

Other information

- Protect the product in this container from excessive heat and direct sun.

Inactive ingredients

Water(Aqua/Eau), Butyloctyl Salicylate, Trisiloxane, Propylheptyl Caprylate, Butylene Glycol, Propanediol, Isododecane, Coco-Caprylate/Caprate, Cetyl Diglyceryl Tris(Trimethylsiloxy)silylethyl Dimethicone, Caprylyl Methicone, Neopentyl Glycol Diheptanoate, Vinyl Dimethicone/Methicone Silsesquioxane Crosspolymer, Lauryl Polyglyceryl-3 Polydimethylsiloxyethyl Dimethicone, Sodium Chloride, Triethoxycaprylylsilane, Triethylhexanoin, 1,2-Hexanediol, Cetyl Dimethicone, Disteardimonium Hectorite, Lauroyl Lysine, Polyglyceryl-2 Dipolyhydroxystearate, Magnesium Sulfate, Lauryl Dimethicone/Polyglycerin-3 Crosspolymer, Caprylyl Glycol, Glyceryl Caprylate, Tocopherol, Dipropylene Glycol, Panthenol, Sodium Citrate, Glycerin, Ceramide NP, Hydrolyzed Hyaluronic Acid, Caesalpinia Spinosa Fruit Extract, Bacillus Ferment, Kappaphycus Alvarezii Extract, Hydroxypropyl Cyclodextrin, Buddleja Officinalis Flower Extract, Centella Asiatica Extract, Houttuynia Cordata Extract, Palmitoyl Tripeptide-5, 7-Dehydrocholesterol, Pinus Pinaster Bark Extract

Questions or comments?

Contact to www.dr-g.com